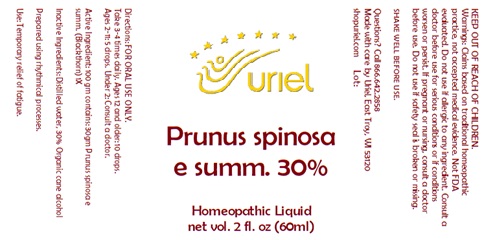 DRUG LABEL: Prunus spinosa e summ 30
NDC: 48951-8376 | Form: LIQUID
Manufacturer: Uriel Pharmacy Inc.
Category: homeopathic | Type: HUMAN OTC DRUG LABEL
Date: 20251119

ACTIVE INGREDIENTS: SLOE 1 [hp_X]/1 mL
INACTIVE INGREDIENTS: WATER; ALCOHOL

Prunus spinosa e summ 30

INDICATIONS AND USAGE

Directions: FOR ORAL USE ONLY.

DOSAGE AND ADMINISTRATION

Take 3-4 times daily. Ages 12 and older: 10 drops. Ages 2-11: 5 drops. Under 2: Consult a doctor.

Active Ingredient: 100 gm contains: 30gm Prunus spinosa e summ. (Blackthorn) 1X

Inactive Ingredients: Distilled water, 30% Organic cane alcohol

PURPOSE

Use: Temporary relief of fatigue.

KEEP OUT OF REACH OF CHILDREN.

WARNINGS

Warnings: Claims based on traditional homeopathic practice, not accepted medical evidence. Not FDA evaluated. Do not use if allergic to any ingredient. Consult a doctor before use for serious conditions or if conditions worsen or persist. If pregnant or nursing, consult a doctor before use. Do not use if safety seal is broken or missing.

Questions? Call 866.642.2858
Made with care by Uriel, East Troy, WI 53120
shopuriel.com